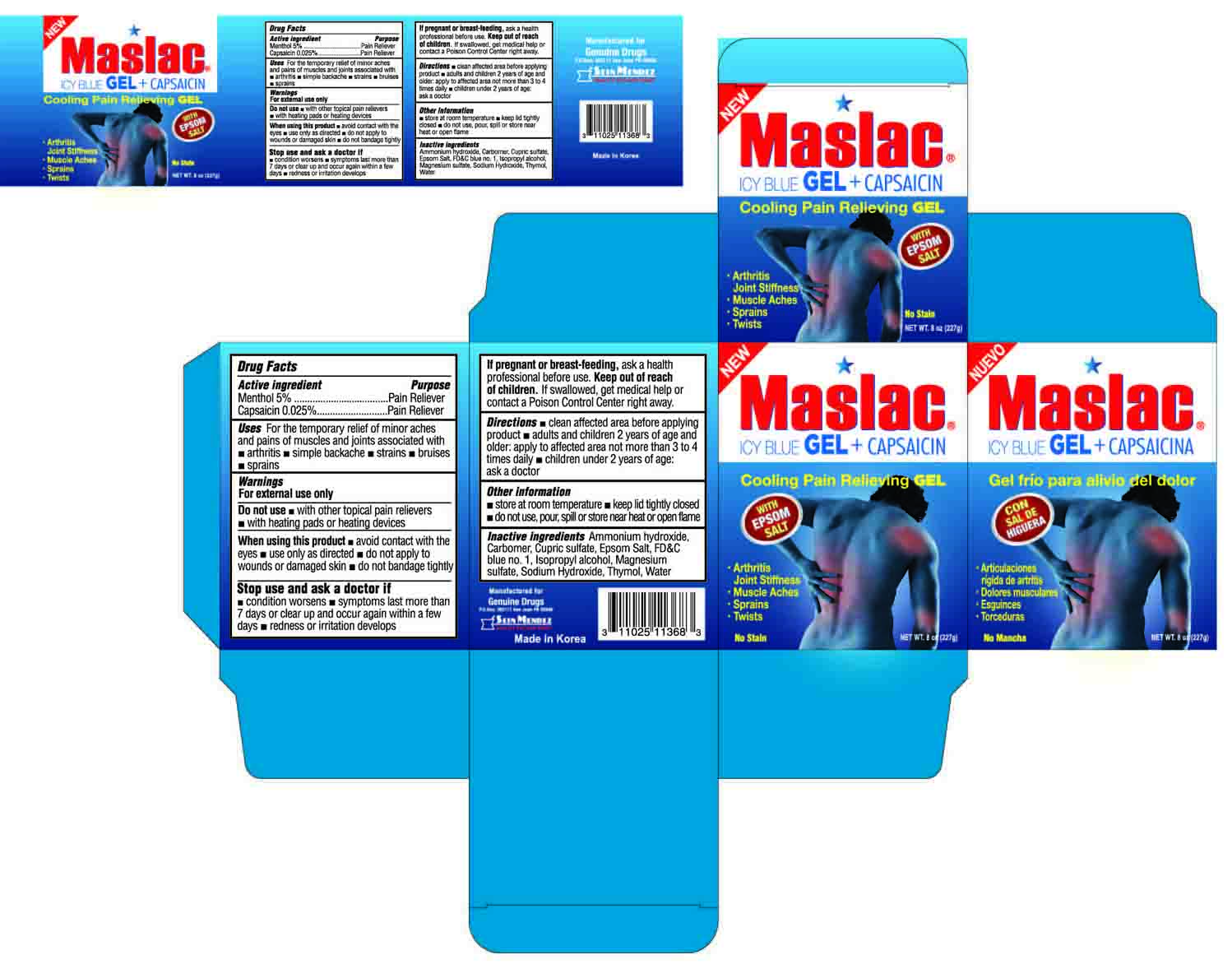 DRUG LABEL: Blue Ice
NDC: 69666-368 | Form: GEL
Manufacturer: Genuine Drugs
Category: otc | Type: HUMAN OTC DRUG LABEL
Date: 20150317

ACTIVE INGREDIENTS: MENTHOL .05 g/1 g; capsaicin .00025 g/1 g
INACTIVE INGREDIENTS: AMMONIA; CUPRIC SULFATE; FD&C BLUE NO. 1; ISOPROPYL ALCOHOL; MAGNESIUM SULFATE; SODIUM HYDROXIDE; THYMOL; WATER

Active Ingredient

Menthol

Capsaicin

Purpose

Pain Reliever

Pain Reliever

Uses

For the temporary relief of minor aches and pains of muscles and joints associated with:

● arthritis ● simple backache ● strains

● bruises ● sprains

Warnings

For external use only

Do not use

- with other topical pain relievers
- with heating pads or heating devices

When using this product

- avoid contact with the eyes
- use only as directed
- do not apply to wounds or damaged skin
- do not bandage tightly

Stop use and ask a doctor if

- condition worsens
- symptoms last more than 7 days or clear up and occur again within a few days
- redness or irritation develops

If pregnant or breast-feeding,

ask a health professional before use

Keep out of reach of children.

If swallowed, get medical help or contact a Poison Control Center right away.

Directions

- clean affected area before applying product
- adults and children 2 years of age and older: apply to affected area not more than 3 to 4 times daily
- children under 2 years of age: ask a doctor

Other information

- store at room temperature
- keep lid tightly closed
- do not use, pour, spill or store near heat or open flame

Inactive ingredients

ammonium hydroxide, carbomer, cupric sulfate, FD&C blue no. 1, isopropyl alcohol, magnesium sulfate, sodium hydroxide, thymol, water

Package label

Maslac Icy Blue Gel + Capsaicin